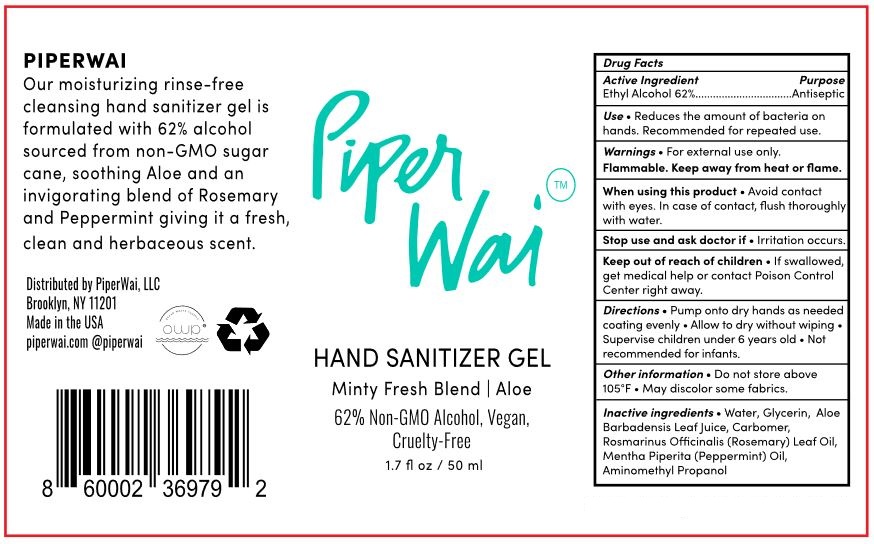 DRUG LABEL: piperwaiHandSanitizerminty
NDC: 81741-111 | Form: SOLUTION
Manufacturer: Piperwai, LLC
Category: otc | Type: HUMAN OTC DRUG LABEL
Date: 20210331

ACTIVE INGREDIENTS: ALCOHOL 62 mL/100 mL
INACTIVE INGREDIENTS: ROSEMARY; AMINOMETHYLPROPANOL; PEPPERMINT OIL; GLYCERIN; ALOE; WATER

This is a hand rub manufactured according to the Temporary Policy for Preparation of Certain Alcohol-Based Hand Rub Products During the Public Health Emergency (CoViD-19); Guidance for Industry.

The hand rub is manufactured using only the following United States Pharmacopoeia (USP) grade ingredients in the preparation of the product (percentage in final product formulation) consistent with World Health Organization (WHO) recommendations:

1. Alcohol (ethanol) (USP or Food Chemical Codex (FCC) grade) (62%, in an aqueous solution denatured according to Alcohol and Tobacco Tax and Trade Bureau regulations in 27 CFR part 20.
2. Glycerol.
3. Sterile distilled water or boiled cold water.

Active Ingredient(s)

Alcohol 62%. Purpose: Antiseptic

Purpose

Antiseptic, Hand Rub

Use

Reduces the amount of bacteria on hands. Recommended for repeated use.

Warnings

For external use only. Flammable. Keep away from heat or flame

Do not use

aviod contact with eyes.
In case of contact, flush thoroughly with water.

When using this product aviod contact with eyes. In case of contact, flush thoroughly with water.
Stop use and ask a doctor if irritation occurs.

Stop use and ask a doctor if irritation or rash occurs.

Keep out of reach of children. If swallowed, get medical help or contact a Poison Control Center right away.

Directions

Pump onto dry hands as needed coating evenly.
Allow to dry without wiping
Supervise children under 6 years old
Not recommended for infants.

Other information

Do not store above 105F

Inactive ingredients

Water, Glycerin, Aloe Barbadensis Leaf Juice, Carbomer, Rosmarinus Officinalis (Rosemary) Leaf Oil, Mentha Piperita (Peppermint) Oil, Aminomethyl Propanol